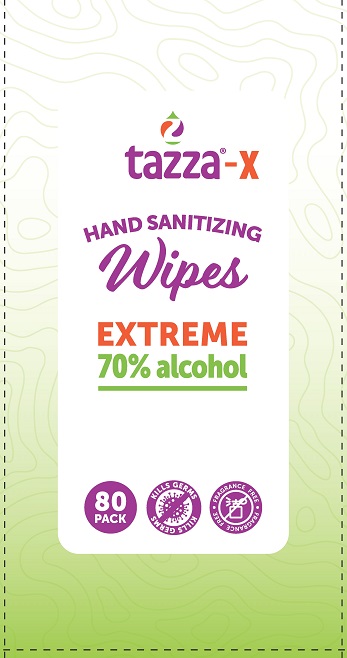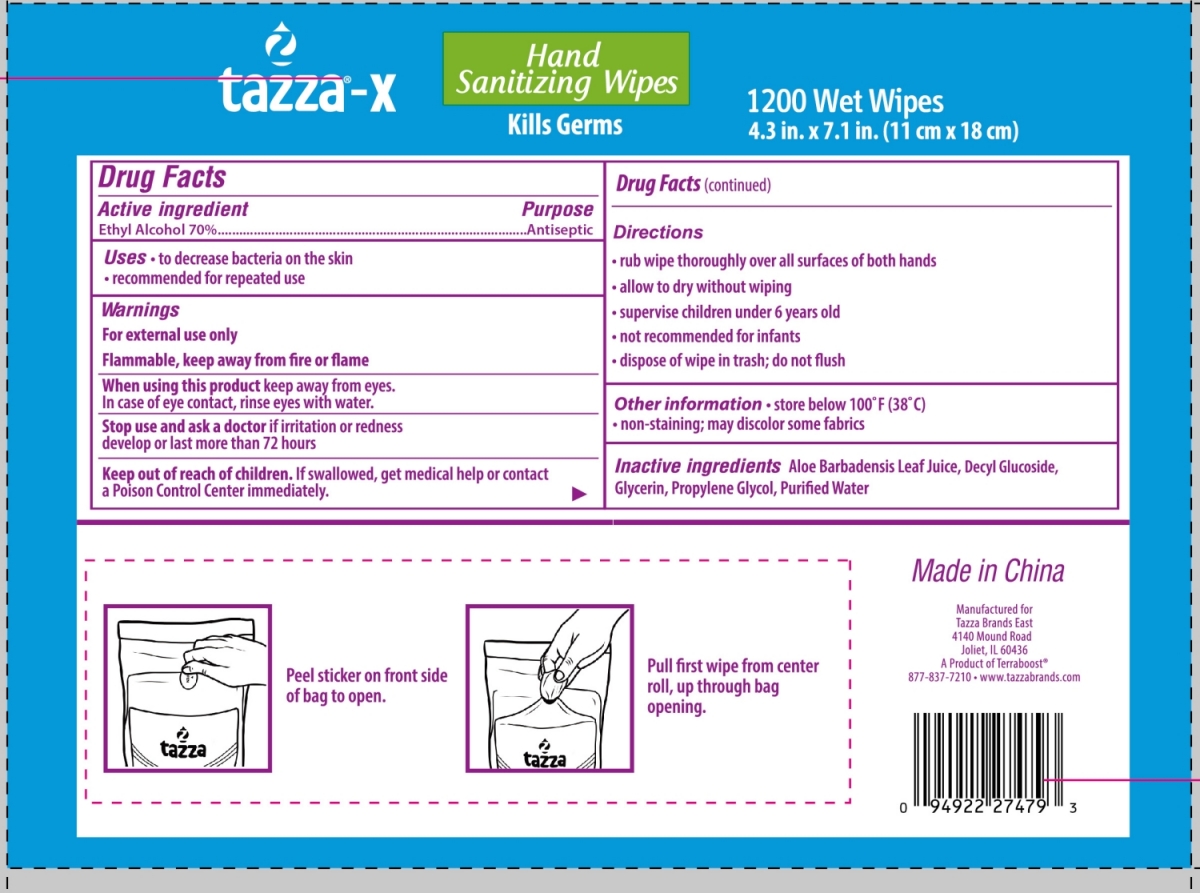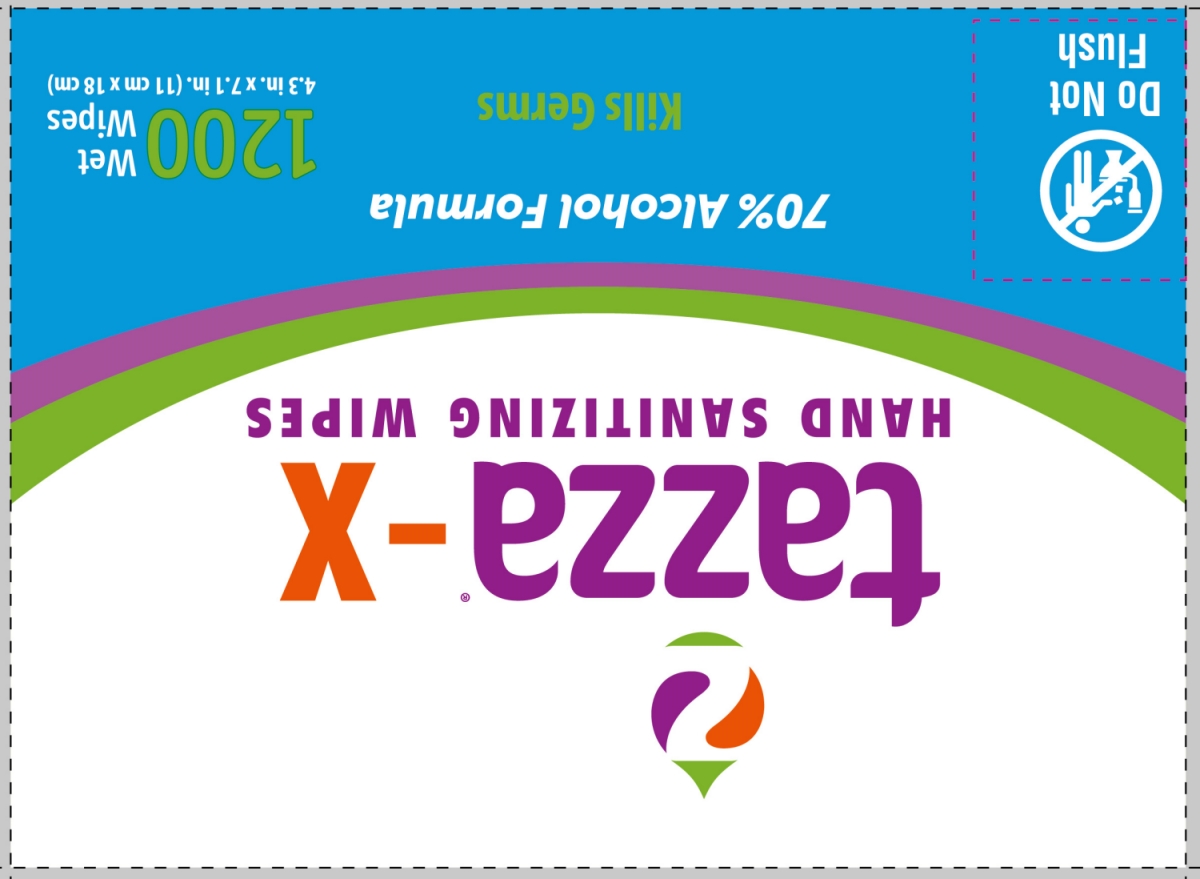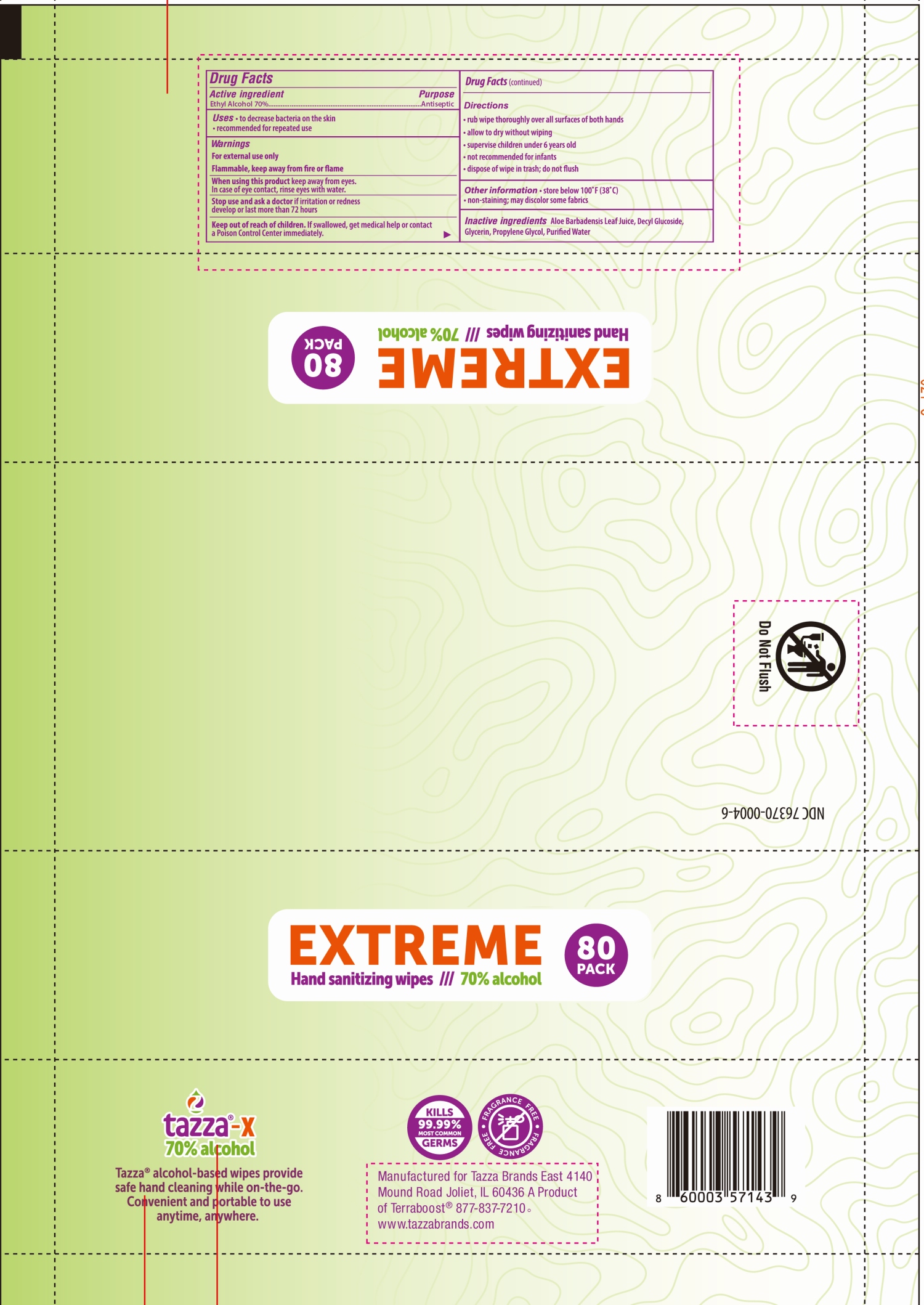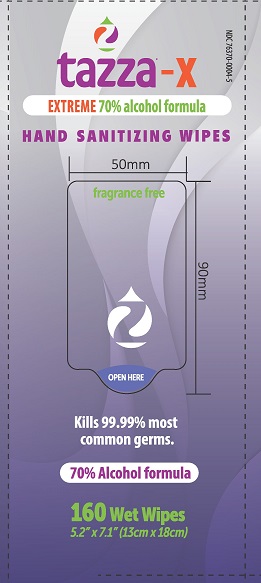 DRUG LABEL: Tazza
NDC: 76370-0004 | Form: CLOTH
Manufacturer: Tazza Brands East Inc.
Category: otc | Type: HUMAN OTC DRUG LABEL
Date: 20251223

ACTIVE INGREDIENTS: ALCOHOL 70 mL/100 mL
INACTIVE INGREDIENTS: WATER; GLYCERIN; ALOE VERA LEAF; DECYL GLUCOSIDE; PROPYLENE GLYCOL

76370-0004 tazza-X HAND SANITIZING WIPES 70% Alcohol Formula

Drug Facts

Active ingredient

Ethyl Alcohol 70%

Purpose

Antiseptic

INDICATIONS AND USAGE

Uses · to decrease bacteria on the skin

· recommended for repeated use

Warnings

For external use only

Flammable, keep away from fire or flame

When using this product keep away from eyes.

In case of eye contact, rinse eyes with water.

Stop use and ask a doctor if irritation or redness

develop or last more than 72 hours

Keep out of reach of children. If swallowed, get medical help or contact

a Poison Control Center immediately.

Directions

· rub wipe thoroughly over all surface of both hands

· allow to dry without wiping

· supervise children under 6 years old

· not recommended for infants

· dispose of wipe in trash; do not flush

Other information • store below 100℉ (38°C)

• non-staining; may discolor some fabrics

INACTIVE INGREDIENT

Inactive ingredientsAloe Barbadensis Leaf Juice, Decyl Glucoside, Glycerin, Propylene Glycol, Purified Water

Manufactured for

Tazza Brands East

4140 Mound Road

Joliet, IL 60436

A Product of Terraboost®

877-837-7210 • www.tazzabrands.com

PACKAGE LABEL

tazza-X HAND SANITIZING WIPES
70% Alcohol Formula
Kills Germs
1200 Wet Wipes
4.3 in. x 7.7 in. (11 cm x 18 cm)
NDC: 76370-0004-3

PACKAGE LABEL

80 PACK

NDC: 76370-0004-6